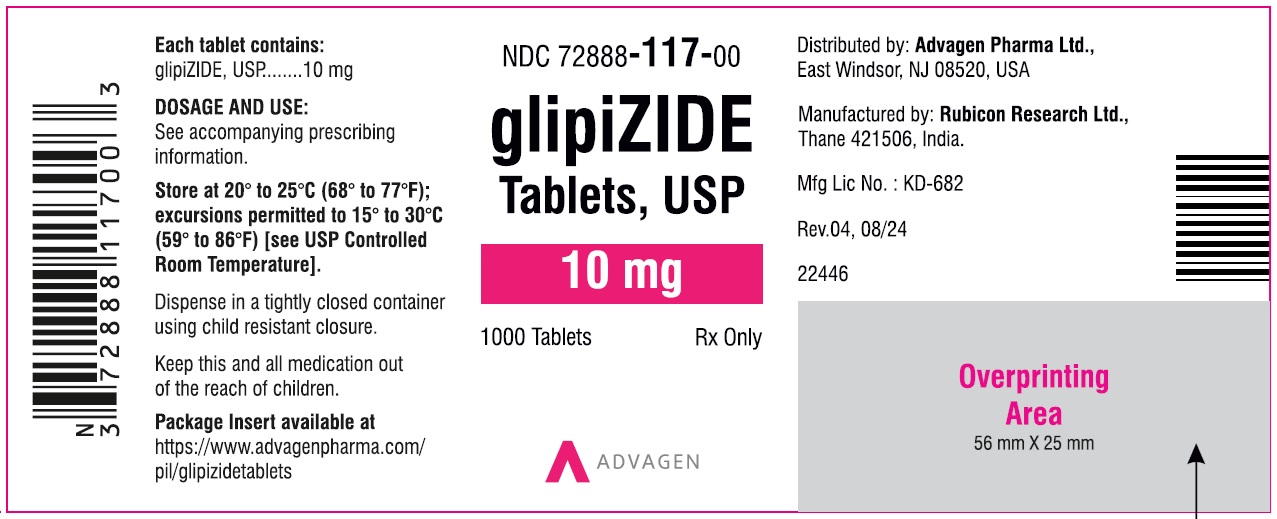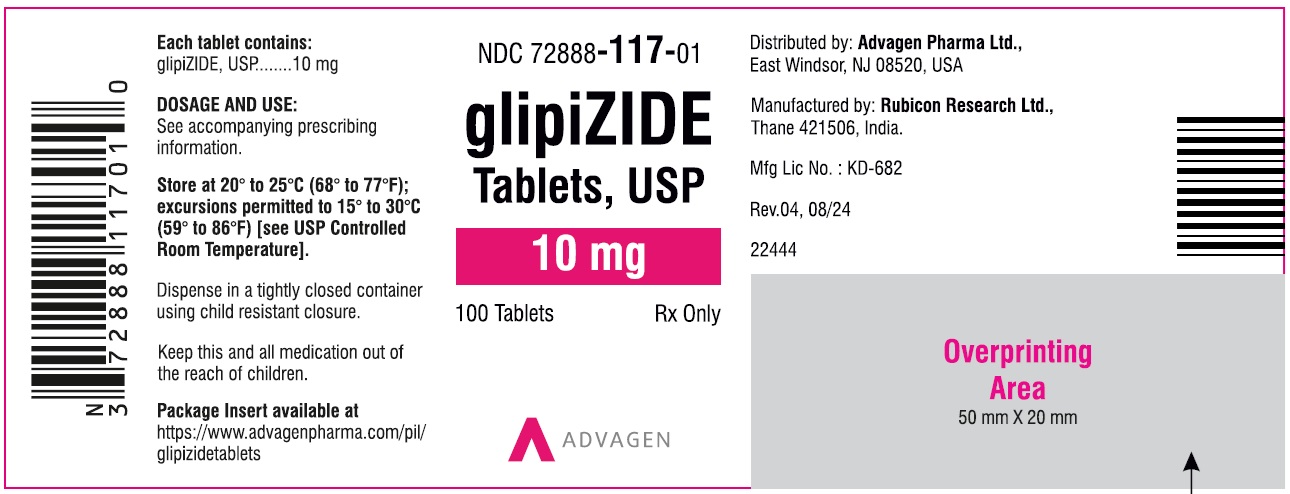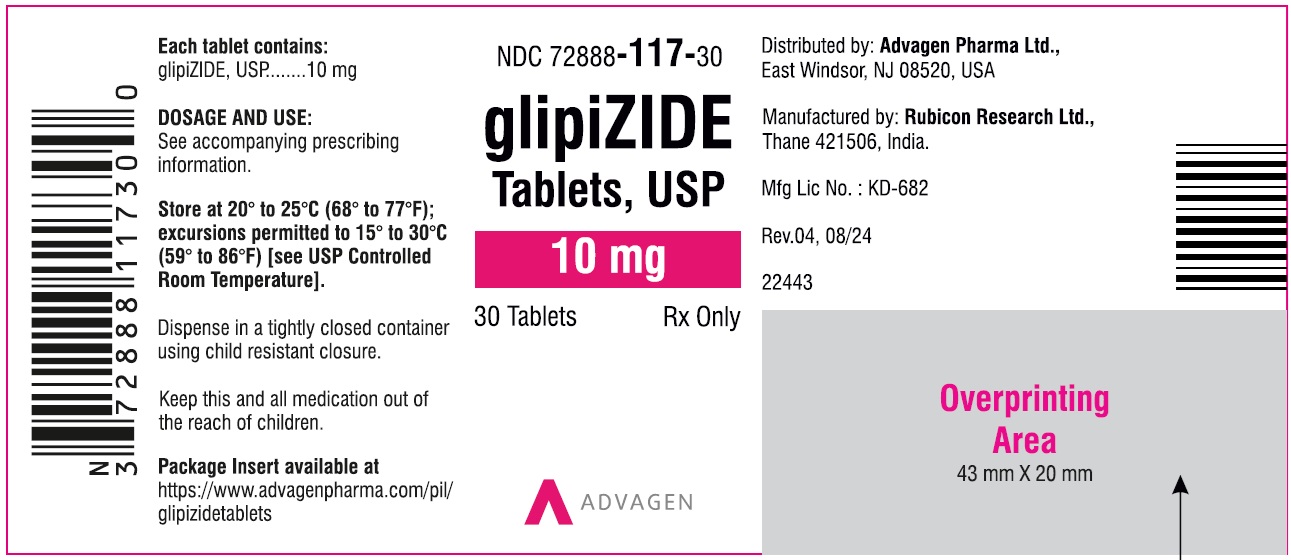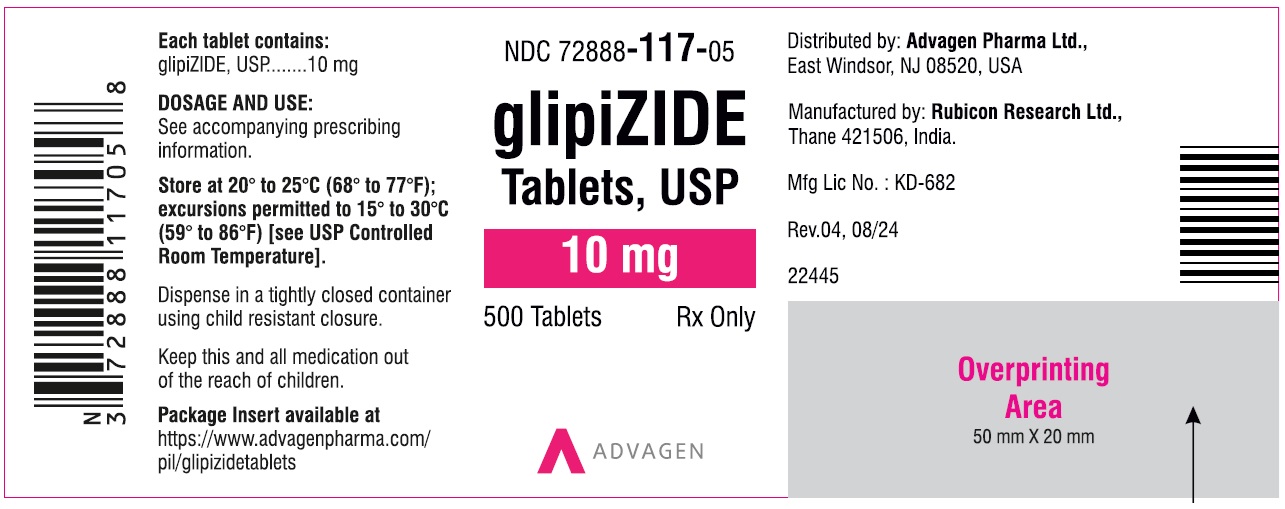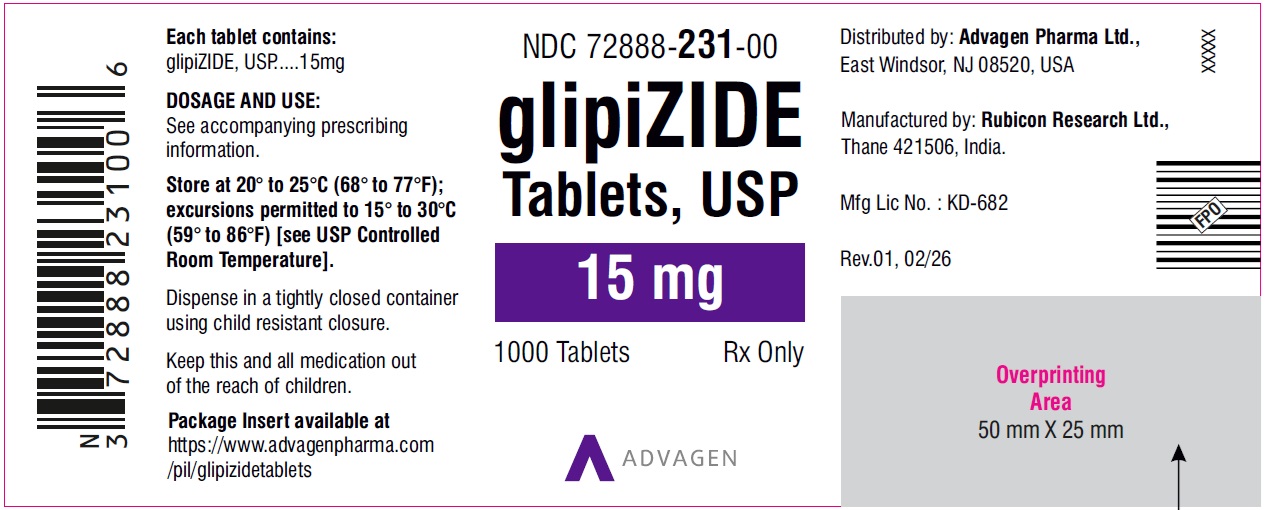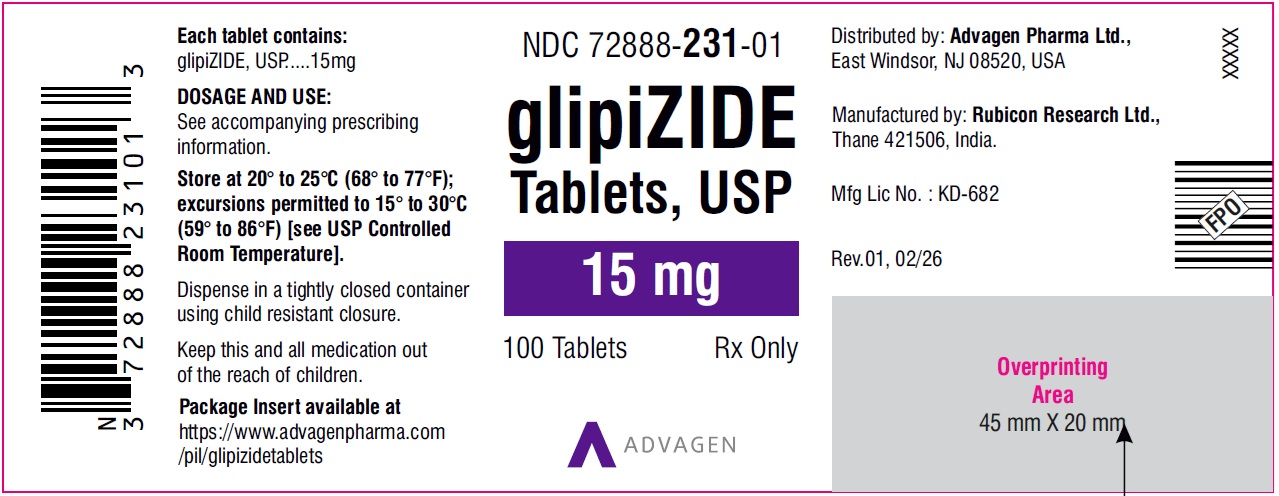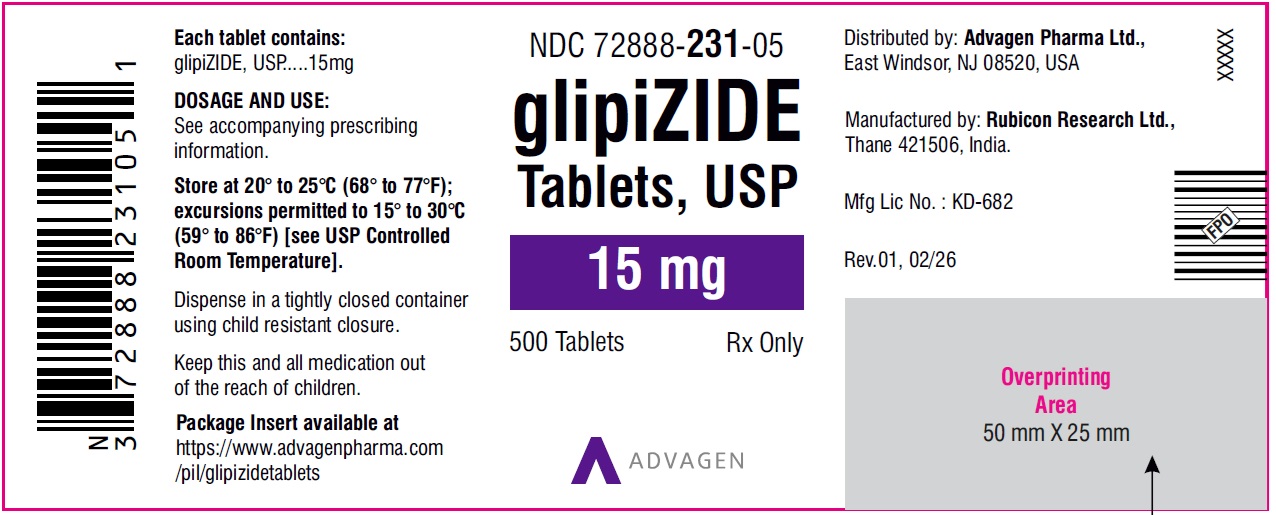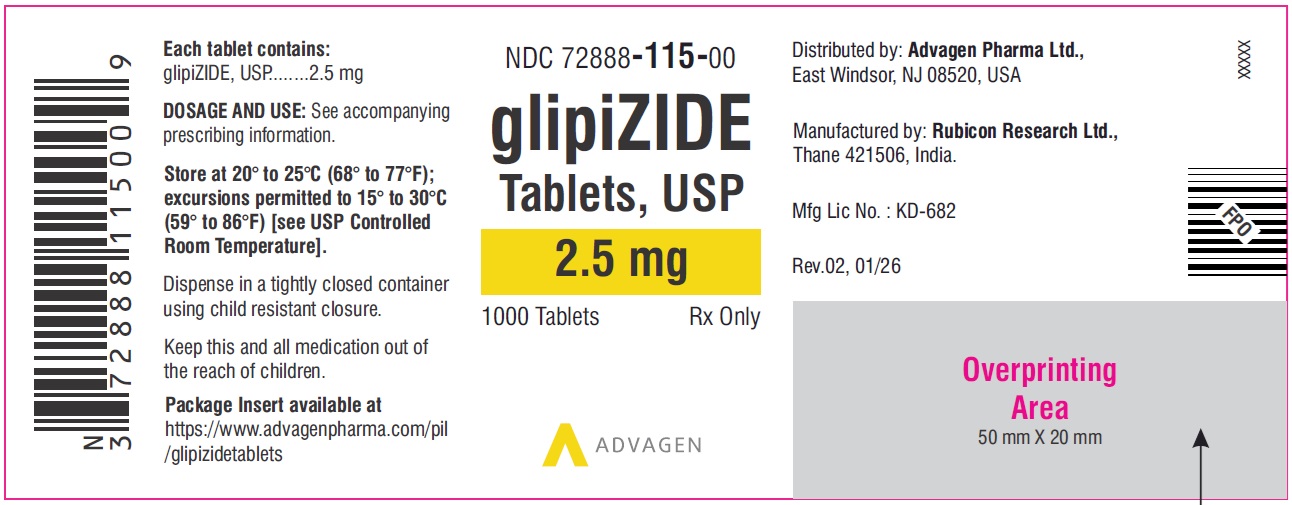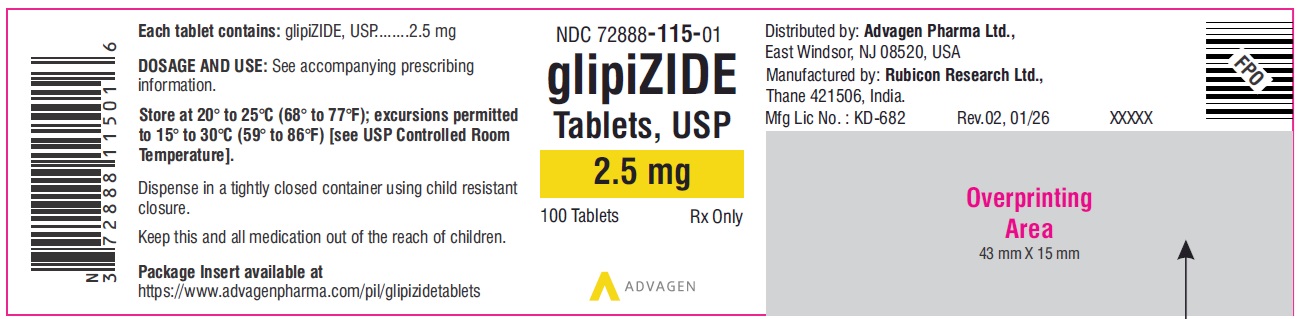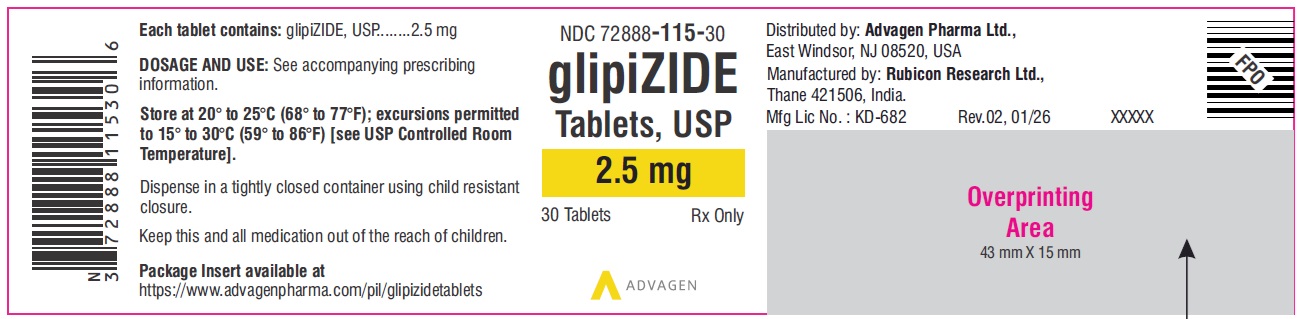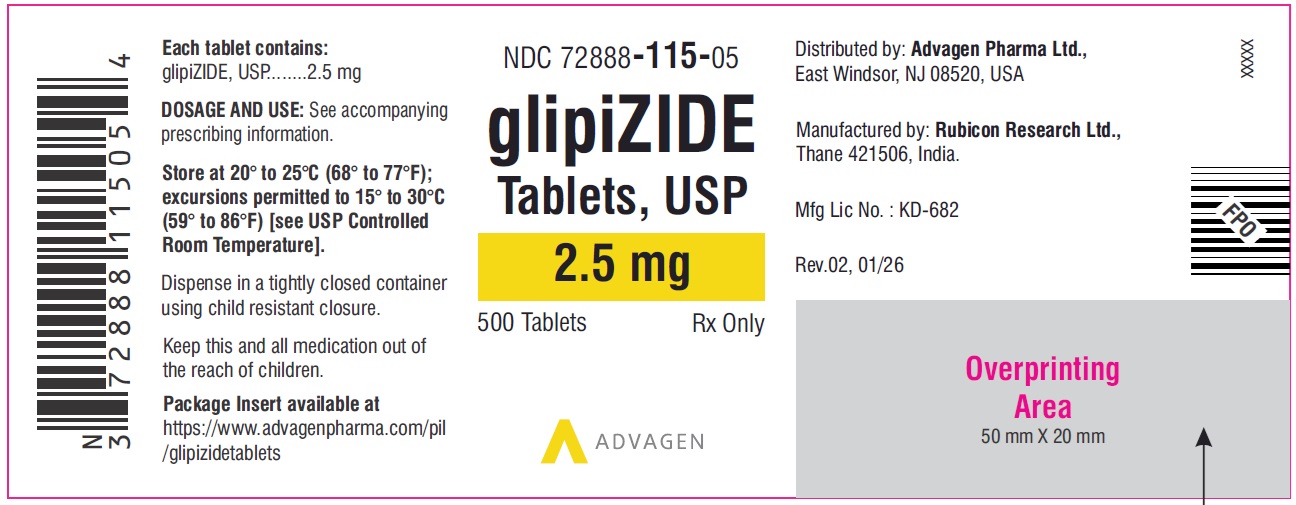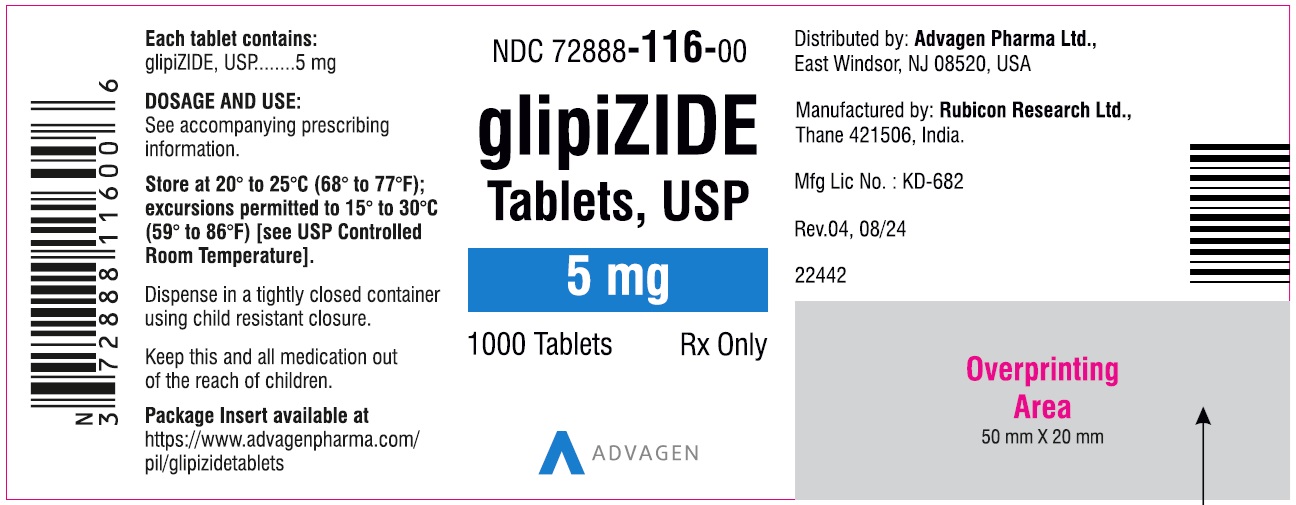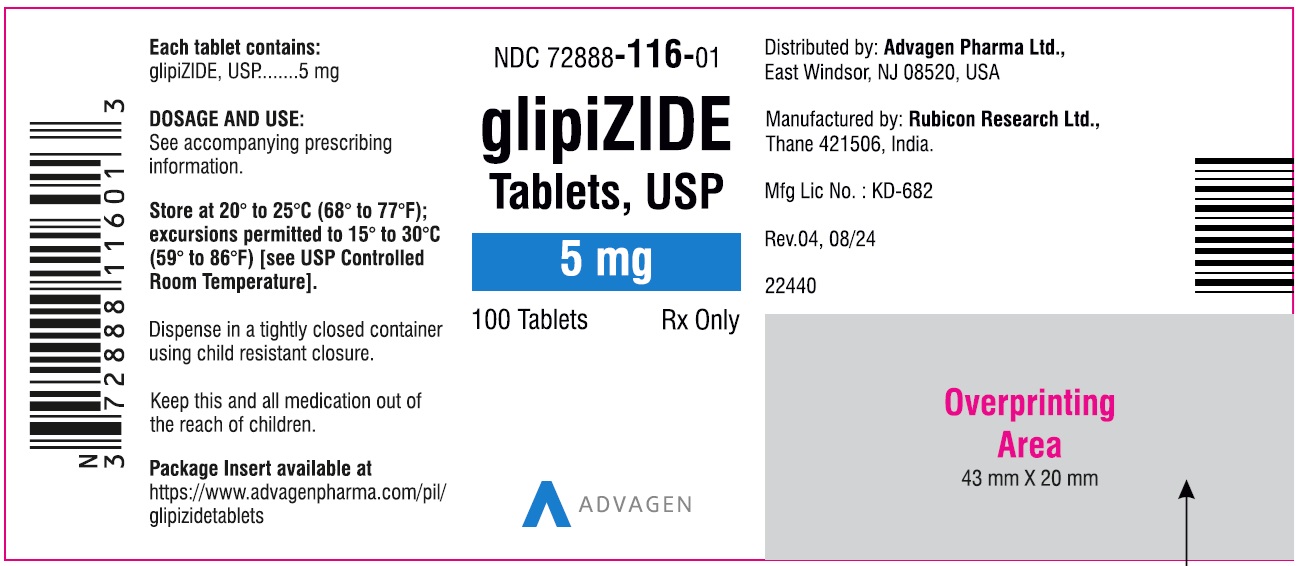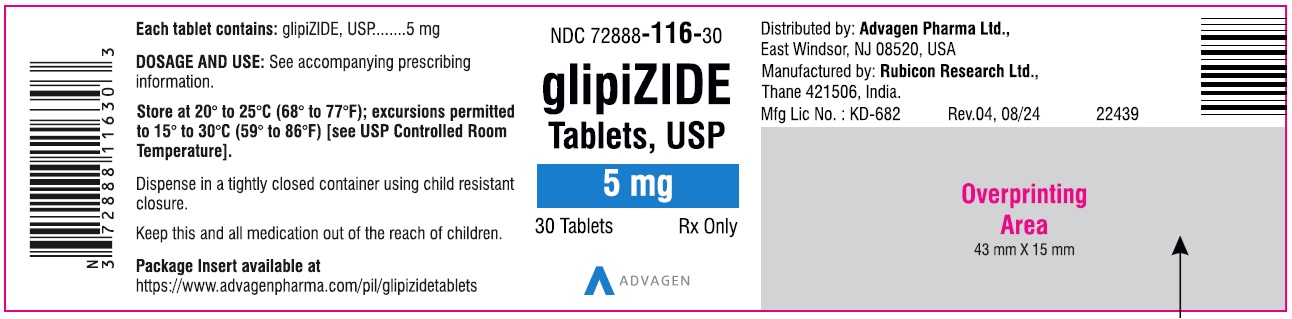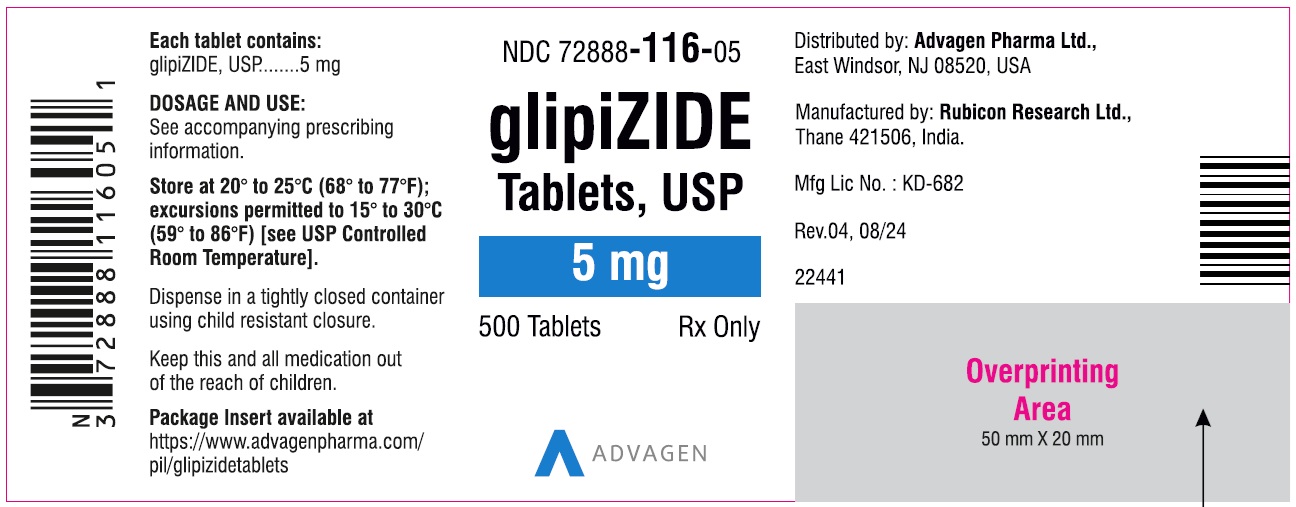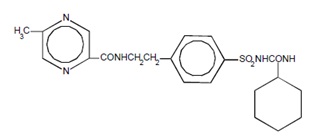 DRUG LABEL: Glipizide
NDC: 72888-115 | Form: TABLET
Manufacturer: Advagen Pharma Limited
Category: prescription | Type: HUMAN PRESCRIPTION DRUG LABEL
Date: 20260224

ACTIVE INGREDIENTS: GLIPIZIDE 2.5 mg/1 1
INACTIVE INGREDIENTS: SILICON DIOXIDE; CROSCARMELLOSE SODIUM; ANHYDROUS LACTOSE; MICROCRYSTALLINE CELLULOSE; STEARIC ACID

Glipizide Tablets, USP
For Oral Use

DESCRIPTION

Glipizide is an oral blood-glucose-lowering drug of the sulfonylurea class.

The Chemical Abstracts name of glipizide is 1-cyclohexyl-3-[[p-[2-(5-methylpyrazine-carboxamido)ethyl]phenyl]sulfonyl]urea. The molecular formula is C21H27N5O4S; the molecular weight is 445.55; the structural formula is shown below:

Glipizide is a whitish, odorless powder with a pKa of 5.9. It is insoluble in water and alcohols, but soluble in 0.1 N NaOH; it is freely soluble in dimethylformamide. Glipizide tablets for oral use are available in 2.5 mg, 5 mg, 10 mg and 15 mg strengths.

Inactive ingredients are: colloidal silicon dioxide; croscarmellose sodium, lactose anhydrous; microcrystalline cellulose and stearic acid.

Meets USP Dissolution test 2.

CLINICAL PHARMACOLOGY

Mechanism of Action:The primary mode of action of glipizide in experimental animals appears to be the stimulation of insulin secretion from the beta cells of pancreatic islet tissue and is thus dependent on functioning beta cells in the pancreatic islets. In humans, glipizide appears to lower the blood glucose acutely by stimulating the release of insulin from the pancreas, an effect dependent upon functioning beta cells in the pancreatic islets. The mechanism by which glipizide lowers blood glucose during long-term administration has not been clearly established. In man, stimulation of insulin secretion by glipizide in response to a meal is undoubtedly of major importance. Fasting insulin levels are not elevated even on long-term glipizide administration, but the postprandial insulin response continues to be enhanced after at least 6 months of treatment. The insulinotropic response to a meal occurs within 30 minutes after an oral dose of glipizide in diabetic patients, but elevated insulin levels do not persist beyond the time of the meal challenge. Extrapancreatic effects may play a part in the mechanism of action of oral sulfonylurea hypoglycemic drugs.

Blood sugar control persists in some patients for up to 24 hours after a single dose of glipizide, even though plasma levels have declined to a small fraction of peak levels by that time (see Pharmacokineticsbelow).

Some patients fail to respond initially, or gradually lose their responsiveness to sulfonylurea drugs, including glipizide. Alternatively, glipizide may be effective in some patients who have not responded or have ceased to respond to other sulfonylureas.

Other Effects:It has been shown that glipizide therapy was effective in controlling blood sugar without deleterious changes in the plasma lipoprotein profiles of patients treated for NIDDM.

In a placebo-controlled, crossover study in normal volunteers, glipizide had no antidiuretic activity and, in fact, led to a slight increase in free water clearance.

Pharmacokinetics:

Gastrointestinal absorption of glipizide in man is uniform, rapid, and essentially complete. Peak plasma concentrations occur 1–3 hours after a single oral dose. The half-life of elimination ranges from 2–4 hours in normal subjects, whether given intravenously or orally. The metabolic and excretory patterns are similar with the two routes of administration, indicating that first-pass metabolism is not significant. Glipizide does not accumulate in plasma on repeated oral administration. Total absorption and disposition of an oral dose was unaffected by food in normal volunteers, but absorption was delayed by about 40 minutes. Thus, glipizide was more effective when administered about 30 minutes before, rather than with, a test meal in diabetic patients. Protein binding was studied in serum from volunteers who received either oral or intravenous glipizide and found to be 98–99% one hour after either route of administration. The apparent volume of distribution of glipizide after intravenous administration was 11 liters, indicative of localization within the extracellular fluid compartment. In mice, no glipizide or metabolites were detectable autoradiographically in the brain or spinal cord of males or females, nor in the fetuses of pregnant females. In another study, however, very small amounts of radioactivity were detected in the fetuses of rats given labelled drug.

The metabolism of glipizide is extensive and occurs mainly in the liver. The primary metabolites are inactive hydroxylation products and polar conjugates and are excreted mainly in the urine. Less than 10% unchanged glipizide is found in the urine.

INDICATIONS AND USAGE

Glipizide tablets are indicated as an adjunct to diet and exercise to improve glycemic control in adults with type 2 diabetes mellitus.

CONTRAINDICATIONS

Glipizide tablets are contraindicated in patients with:

1. Known hypersensitivity to the drug.
2. Type 1 diabetes mellitus, diabetic ketoacidosis, with or without coma. This condition should be treated with insulin.

WARNINGS

SPECIAL WARNING ON INCREASED RISK OF CARDIOVASCULAR MORTALITY

The administration of oral hypoglycemic drugs has been reported to be associated with increased cardiovascular mortality as compared to treatment with diet alone or diet plus insulin. This warning is based on the study conducted by the University Group Diabetes Program (UGDP), a long-term prospective clinical trial designed to evaluate the effectiveness of glucose-lowering drugs in preventing or delaying vascular complications in patients with non-insulin-dependent diabetes. The study involved 823 patients who were randomly assigned to one of four treatment groups (Diabetes, 19, supp. 2: 747–830, 1970).

UGDP reported that patients treated for 5 to 8 years with diet plus a fixed dose of tolbutamide (1.5 grams per day) had a rate of cardiovascular mortality approximately 2½ times that of patients treated with diet alone. A significant increase in total mortality was not observed, but the use of tolbutamide was discontinued based on the increase in cardiovascular mortality, thus limiting the opportunity for the study to show an increase in overall mortality. Despite controversy regarding the interpretation of these results, the findings of the UGDP study provide an adequate basis for this warning. The patient should be informed of the potential risks and advantages of glipizide and of alternative modes of therapy.

Although only one drug in the sulfonylurea class (tolbutamide) was included in this study, it is prudent from a safety standpoint to consider that this warning may also apply to other oral hypoglycemic drugs in this class, in view of their close similarities in mode of action and chemical structure.

PRECAUTIONS

General

Macrovascular Outcomes:There have been no clinical studies establishing conclusive evidence of macrovascular risk reduction with glipizide or any other anti-diabetic drug.

Renal and Hepatic Disease:The metabolism and excretion of glipizide may be slowed in patients with impaired renal and/or hepatic function. If hypoglycemia should occur in such patients, it may be prolonged and appropriate management should be instituted.

Hypoglycemia:All sulfonylurea drugs are capable of producing severe hypoglycemia. Proper patient selection, dosage, and instructions are important to avoid hypoglycemic episodes. Renal or hepatic insufficiency may cause elevated blood levels of glipizide and the latter may also diminish gluconeogenic capacity, both of which increase the risk of serious hypoglycemic reactions. Elderly, debilitated or malnourished patients, and those with adrenal or pituitary insufficiency, are particularly susceptible to the hypoglycemic action of glucose-lowering drugs. Hypoglycemia may be difficult to recognize in the elderly, and in people who are taking beta-adrenergic blocking drugs. Hypoglycemia is more likely to occur when caloric intake is deficient, after severe or prolonged exercise, when alcohol is ingested, or when more than one glucose-lowering drug is used.

Loss of Control of Blood Glucose:When a patient stabilized on any diabetic regimen is exposed to stress such as fever, trauma, infection, or surgery, a loss of control may occur. At such times, it may be necessary to discontinue glipizide and administer insulin.

The effectiveness of any oral hypoglycemic drug, including glipizide, in lowering blood glucose to a desired level decreases in many patients over a period of time, which may be due to progression of the severity of the diabetes or to diminished responsiveness to the drug. This phenomenon is known as secondary failure, to distinguish it from primary failure in which the drug is ineffective in an individual patient when first given.

Hemolytic Anemia:Treatment of patients with glucose 6-phosphate dehydrogenase (G6PD) deficiency with sulfonylurea agents can lead to hemolytic anemia. Because glipizide belongs to the class of sulfonylurea agents, caution should be used in patients with G6PD deficiency and a non-sulfonylurea alternative should be considered. In post-marketing reports, hemolytic anemia has also been reported in patients who did not have known G6PD deficiency.

Laboratory Tests

Blood and urine glucose should be monitored periodically. Measurement of glycosylated hemoglobin may be useful.

Information for Patients

Patients should be informed of the potential risks and advantages of glipizide and of alternative modes of therapy. They should also be informed about the importance of adhering to dietary instructions, of a regular exercise program, and of regular testing of urine and/or blood glucose.

The risks of hypoglycemia, its symptoms and treatment, and conditions that predispose to its development should be explained to patients and responsible family members. Primary and secondary failure should also be explained.
Physician Counseling Information for Patients
In initiating treatment for type 2 diabetes, diet should be emphasized as the primary form of treatment. Caloric restriction and weight loss are essential in the obese diabetic patient. Proper dietary management alone may be effective in controlling the blood glucose and symptoms of hyperglycemia. The importance of regular physical activity should also be stressed, and cardiovascular risk factors should be identified and corrective measures taken where possible. Use of glipizide or other antidiabetic medications must be viewed by both the physician and patient as a treatment in addition to diet and not as a substitution or as a convenient mechanism for avoiding dietary restraint. Furthermore, loss of blood glucose control on diet alone may be transient, thus requiring only short-term administration of glipizide tablets or other antidiabetic medications. Maintenance or discontinuation of glipizide tablets or other antidiabetic medications should be based on clinical judgment using regular clinical and laboratory evaluations.

DRUG INTERACTIONS

Drug Interactions:The hypoglycemic action of sulfonylureas may be potentiated by certain drugs including nonsteroidal anti-inflammatory agents, some azoles, and other drugs that are highly protein bound, salicylates, sulfonamides, chloramphenicol, probenecid, coumarins, monoamine oxidase inhibitors, quinolones and beta adrenergic blocking agents. When such drugs are administered to a patient receiving glipizide, the patient should be observed closely for hypoglycemia. When such drugs are withdrawn from a patient receiving glipizide, the patient should be observed closely for loss of control. In vitro binding studies with human serum proteins indicate that glipizide binds differently than tolbutamide and does not interact with salicylate or dicumarol. However, caution must be exercised in extrapolating these findings to the clinical situation and in the use of glipizide with these drugs.

Certain drugs tend to produce hyperglycemia and may lead to loss of control. These drugs include the thiazides and other diuretics, corticosteroids, phenothiazines, thyroid products, estrogens, oral contraceptives, phenytoin, nicotinic acid, sympathomimetics, calcium channel blocking drugs, and isoniazid. When such drugs are administered to a patient receiving glipizide, the patient should be closely observed for loss of control. When such drugs are withdrawn from a patient receiving glipizide, the patient should be observed closely for hypoglycemia.

A potential interaction between oral miconazole and oral hypoglycemic agents leading to severe hypoglycemia has been reported. Whether this interaction also occurs with the intravenous, topical, or vaginal preparations of miconazole is not known. The effect of concomitant administration of DIFLUCAN®(fluconazole) and glipizide has been demonstrated in a placebo-controlled crossover study in normal volunteers. All subjects received glipizide alone and following treatment with 100 mg of DIFLUCAN as a single daily oral dose for 7 days. The mean percentage increase in the glipizide AUC after fluconazole administration was 56.9% (range: 35 to 81).

In studies assessing the effect of colesevelam on the pharmacokinetics of glipizide ER in healthy volunteers, reductions in glipizide AUC0–∞and Cmaxof 12% and 13%, respectively were observed when colesevelam was coadministered with glipizide ER. When glipizide ER was administered 4 hours prior to colesevelam, there was no significant change in glipizide AUC0–∞or Cmax,-4% and 0%, respectively. Therefore, glipizide should be administered at least 4 hours prior to colesevelam to ensure that colesevelam does not reduce the absorption of glipizide.

CARCINOGENESIS AND MUTAGENESIS AND IMPAIRMENT OF FERTILITY

Carcinogenesis, Mutagenesis, Impairment of Fertility:A twenty month study in rats and an eighteen month study in mice at doses up to 75 times the maximum human dose revealed no evidence of drug-related carcinogenicity. Bacterial and in vivo mutagenicity tests were uniformly negative. Studies in rats of both sexes at doses up to 75 times the human dose showed no effects on fertility.

Pregnancy:

Glipizide was found to be mildly fetotoxic in rat reproductive studies at all dose levels (5–50 mg/kg). This fetotoxicity has been similarly noted with other sulfonylureas, such as tolbutamide and tolazamide. The effect is perinatal and believed to be directly related to the pharmacologic (hypoglycemic) action of glipizide. In studies in rats and rabbits, no teratogenic effects were found. There are no adequate and well controlled studies in pregnant women. Glipizide should be used during pregnancy only if the potential benefit justifies the potential risk to the fetus.

Because recent information suggests that abnormal blood glucose levels during pregnancy are associated with a higher incidence of congenital abnormalities, many experts recommend that insulin be used during pregnancy to maintain blood glucose levels as close to normal as possible.

NONTERATOGENIC EFFECTS

Nonteratogenic Effects:Prolonged severe hypoglycemia (4 to 10 days) has been reported in neonates born to mothers who were receiving a sulfonylurea drug at the time of delivery. This has been reported more frequently with the use of agents with prolonged half-lives. If glipizide is used during pregnancy, it should be discontinued at least one month before the expected delivery date.

NURSING MOTHERS

Nursing Mothers:Although it is not known whether glipizide is excreted in human milk, some sulfonylurea drugs are known to be excreted in human milk. Because the potential for hypoglycemia in nursing infants may exist, a decision should be made whether to discontinue nursing or to discontinue the drug, taking into account the importance of the drug to the mother. If the drug is discontinued and if diet alone is inadequate for controlling blood glucose, insulin therapy should be considered.

PEDIATRIC USE

Pediatric Use:Safety and effectiveness in children have not been established.

GERIATRIC USE

Geriatric Use:A determination has not been made whether controlled clinical studies of glipizide included sufficient numbers of subjects aged 65 and over to define a difference in response from younger subjects. Other reported clinical experience has not identified differences in responses between the elderly and younger patients. In general, dose selection for an elderly patient should be cautious, usually starting at the low end of the dosing range, reflecting the greater frequency of decreased hepatic, renal, or cardiac function, and of concomitant disease or other drug therapy.

ADVERSE REACTIONS

In U.S. and foreign controlled studies, the frequency of serious adverse reactions reported was very low. Of 702 patients, 11.8% reported adverse reactions and in only 1.5% was glipizide discontinued.

Hypoglycemia:See PRECAUTIONSand OVERDOSAGEsections.

Gastrointestinal:Gastrointestinal disturbances are the most common reactions. Gastrointestinal complaints were reported with the following approximate incidence: nausea and diarrhea, one in seventy; constipation and gastralgia, one in one hundred. They appear to be dose-related and may disappear on division or reduction of dosage. Cholestatic jaundice may occur rarely with sulfonylureas: glipizide should be discontinued if this occurs.

Dermatologic:Allergic skin reactions including erythema, morbilliform or maculopapular eruptions, urticaria, pruritus, and eczema have been reported in about one in seventy patients. These may be transient and may disappear despite continued use of glipizide; if skin reactions persist, the drug should be discontinued. Porphyria cutanea tarda and photosensitivity reactions have been reported with sulfonylureas.

Hematologic:Leukopenia, agranulocytosis, thrombocytopenia, hemolytic anemia (see PRECAUTIONS), aplastic anemia, and pancytopenia have been reported with sulfonylureas.

Metabolic:Hepatic porphyria and disulfiram-like reactions have been reported with sulfonylureas. In the mouse, glipizide pretreatment did not cause an accumulation of acetaldehyde after ethanol administration. Clinical experience to date has shown that glipizide has an extremely low incidence of disulfiram-like alcohol reactions.

Endocrine Reactions:Cases of hyponatremia and the syndrome of inappropriate antidiuretic hormone (SIADH) secretion have been reported with this and other sulfonylureas.

Miscellaneous:Dizziness, drowsiness, and headache have each been reported in about one in fifty patients treated with glipizide. They are usually transient and seldom require discontinuance of therapy.

LABORATORY TESTS

Laboratory Tests:The pattern of laboratory test abnormalities observed with glipizide was similar to that for other sulfonylureas. Occasional mild to moderate elevations of SGOT, LDH, alkaline phosphatase, BUN, and creatinine were noted. One case of jaundice was reported. The relationship of these abnormalities to glipizide is uncertain, and they have rarely been associated with clinical symptoms.

Post-Marketing Experience The following adverse events have been reported in post-marketing surveillance:

Hepatobiliary:Cholestatic and hepatocellular forms of liver injury accompanied by jaundice have been reported rarely in association with glipizide; glipizide should be discontinued if this occurs.

OVERDOSAGE

There is no well documented experience with glipizide overdosage. The acute oral toxicity was extremely low in all species tested (LD50greater than 4 g/kg).

Overdosage of sulfonylureas, including glipizide, can produce hypoglycemia. Mild hypoglycemic symptoms without loss of consciousness or neurologic findings should be treated aggressively with oral glucose and adjustments in drug dosage and/or meal patterns. Close monitoring should continue until the physician is assured that the patient is out of danger. Severe hypoglycemic reactions with coma, seizure, or other neurological impairment occur infrequently, but constitute medical emergencies requiring immediate hospitalization. If hypoglycemic coma is diagnosed or suspected, the patient should be given a rapid intravenous injection of concentrated (50%) glucose solution. This should be followed by a continuous infusion of a more dilute (10%) glucose solution at a rate that will maintain the blood glucose at a level above 100 mg/dL. Patients should be closely monitored for a minimum of 24 to 48 hours since hypoglycemia may recur after apparent clinical recovery. Clearance of glipizide from plasma would be prolonged in persons with liver disease. Because of the extensive protein binding of glipizide, dialysis is unlikely to be of benefit.

DOSAGE AND ADMINISTRATION

There is no fixed dosage regimen for the management of diabetes mellitus with glipizide or any other hypoglycemic agent. In addition to the usual monitoring of urinary glucose, the patient's blood glucose must also be monitored periodically to determine the minimum effective dose for the patient; to detect primary failure, i.e., inadequate lowering of blood glucose at the maximum recommended dose of medication; and to detect secondary failure, i.e., loss of an adequate blood-glucose-lowering response after an initial period of effectiveness. Glycosylated hemoglobin levels may also be of value in monitoring the patient's response to therapy.

Short-term administration of glipizide tablets may be sufficient during periods of transient loss of control in patients usually controlled well on diet.

In general, glipizide tablets should be given approximately 30 minutes before a meal to achieve the greatest reduction in postprandial hyperglycemia.

Initial Dose:The recommended starting dose is 5 mg, given before breakfast. Geriatric patients or those with liver disease may be started on 2.5 mg.

Titration:Dosage adjustments should ordinarily be in increments of 2.5–5 mg, as determined by blood glucose response. At least several days should elapse between titration steps. If response to a single dose is not satisfactory, dividing that dose may prove effective. The maximum recommended once daily dose is 15 mg. Doses above 15 mg should ordinarily be divided and given before meals of adequate caloric content. The maximum recommended total daily dose is 40 mg.

Maintenance:Some patients may be effectively controlled on a once-a-day regimen, while others show better response with divided dosing. Total daily doses above 15 mg should ordinarily be divided. Total daily doses above 30 mg have been safely given on a b.i.d. basis to long-term patients.

In elderly patients, debilitated or malnourished patients, and patients with impaired renal or hepatic function, the initial and maintenance dosing should be conservative to avoid hypoglycemic reactions (see PRECAUTIONSsection).

Patients Receiving Insulin:As with other sulfonylurea-class hypoglycemics, many stable non-insulin-dependent diabetic patients receiving insulin may be safely placed on Glipizide tablets. When transferring patients from insulin to glipizide tablets, the following general guidelines should be considered:

- For patients whose daily insulin requirement is 20 units or less, insulin may be discontinued and glipizide therapy may begin at usual dosages. Several days should elapse between glipizide titration steps.
- For patients whose daily insulin requirement is greater than 20 units, the insulin dose should be reduced by 50% and glipizide therapy may begin at usual dosages. Subsequent reductions in insulin dosage should depend on individual patient response. Several days should elapse between glipizide titration steps.

During the insulin withdrawal period, the patient should test urine samples for sugar and ketone bodies at least three times daily. Patients should be instructed to contact the prescriber immediately if these tests are abnormal. In some cases, especially when patient has been receiving greater than 40 units of insulin daily, it may be advisable to consider hospitalization during the transition period.

Patients Receiving Other Oral Hypoglycemic Agents:As with other sulfonylurea-class hypoglycemics, no transition period is necessary when transferring patients to glipizide. Patients should be observed carefully (1–2 weeks) for hypoglycemia when being transferred from longer half-life sulfonylureas (e.g., chlorpropamide) to glipizide due to potential overlapping of drug effect.

When colesevelam is coadministered with glipizide ER, maximum plasma concentration and total exposure to glipizide is reduced. Therefore, glipizide tablets should be administered at least 4 hours prior to colesevelam.

HOW SUPPLIED

Glipizide tablets 2.5 mg are round, white to off-white, uncoated tablets, debossed on one side and Ʌ on other side. They are supplied as follows:

I1

NDC 72888-115-30, bottles of 30.

NDC 72888-115-01, bottles of 100.

NDC 72888-115-05, bottles of 500.

NDC 72888-115-00, bottles of 1000.

Glipizide tablets 5 mg are Round, white to off-white, uncoated tablets, debossed Λ on one side and break line on other side. They are supplied as follows:
I2

NDC 72888-116-30, bottles of 30.

NDC 72888-116-01, bottles of 100.

NDC 72888-116-05, bottles of 500.

NDC 72888-116-00, bottles of 1000.

Glipizide tablets 10 mg are Round, white to off-white, uncoated tablets, debossed Λ on one side and break line on other side. They are supplied as follows:
I4

NDC 72888-117-30, bottles of 30.

NDC 72888-117-01, bottles of 100.

NDC 72888-117-05, bottles of 500.

NDC 72888-117-00, bottles of 1000.

Glipizide tablets 15 mg are Round, white to off-white, uncoated tablets, debossed Λ on one side and break line on other side. They are supplied as follows:
I11

NDC 72888-231-01, bottles of 100.

NDC 72888-231-05, bottles of 500.

NDC 72888-231-00, bottles of 1000.

RECOMMENDED STORAGE:

Store at 20° to 25°C (68° to 77°F); excursions permitted to 15° to 30°C (59° to 86°F) [see USP Controlled Room Temperature].

Dispense in a tightly closed container using child resistant closure.

All trademarks are the property of their respective owners.

Manufactured by:
Rubicon Research Limited
Thane, 421506 India

Distributed by:
Advagen Pharma Ltd
East Windsor, NJ 08520, USA.

Revision:04, 02/2026

PACKAGE LABEL-PRINCIPAL DISPLAY PANEL

Glipizide Tablets 2.5 mg - NDC 72888-115-30 - 30 Tablets Label

Glipizide Tablets 2.5 mg - NDC 72888-115-01 - 100 Tablets Label

Glipizide Tablets 2.5 mg - NDC 72888-115-05 - 500 Tablets Label

Glipizide Tablets 2.5 mg - NDC 72888-115-00 - 1000 Tablets Label

Glipizide Tablets 5 mg - NDC 72888-116-30 - 30 Tablets Label

Glipizide Tablets 5 mg - NDC 72888-116-01 - 100 Tablets Label

Glipizide Tablets 5 mg - NDC 72888-116-05 - 500 Tablets Label

Glipizide Tablets 5 mg - NDC 72888-116-00 - 1000 Tablets Label

Glipizide Tablets 10 mg - NDC 72888-117-30 - 30 Tablets Label

Glipizide Tablets 10 mg - NDC 72888-117-01 - 100 Tablets Label

Glipizide Tablets 10 mg - NDC 72888-117-05 - 500 Tablets Label

Glipizide Tablets 10 mg - NDC 72888-117-00 - 1000 Tablets Label

Glipizide Tablets 15 mg - NDC 72888-231-01 - 100 Tablets Label

Glipizide Tablets 15 mg - NDC 72888-231-05 - 500 Tablets Label

Glipizide Tablets 15 mg - NDC 72888-231-00 - 1000 Tablets Label